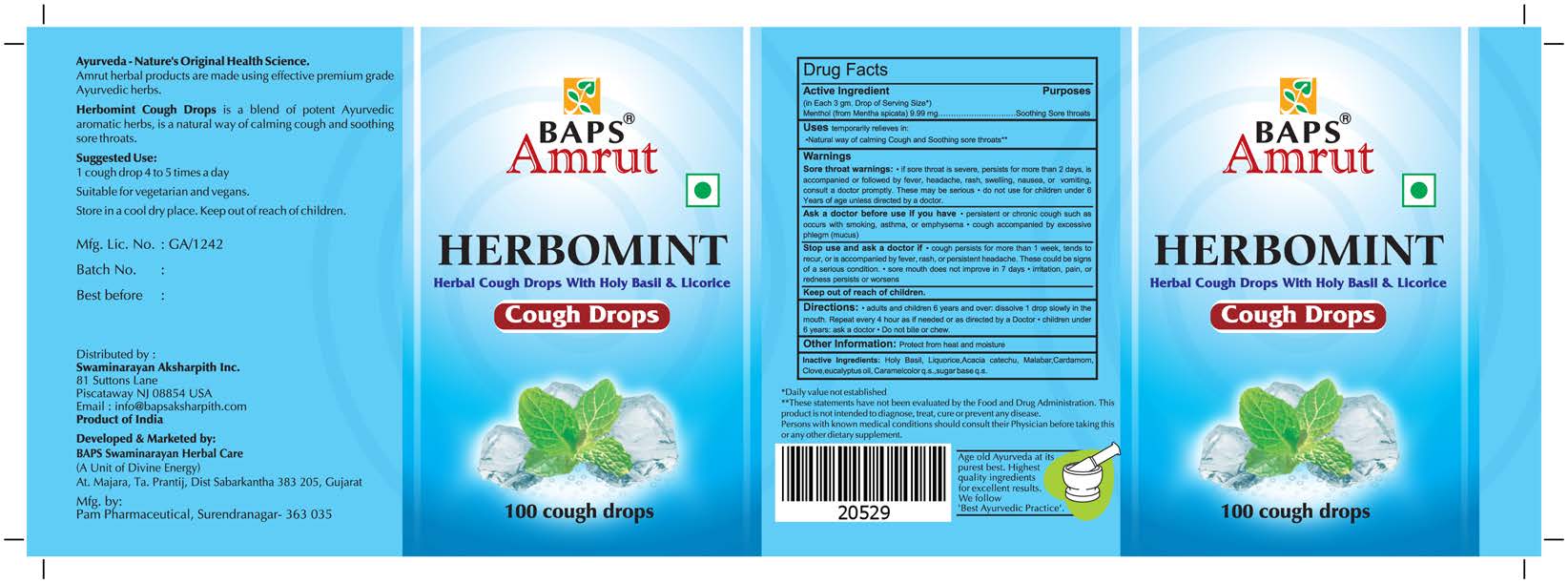 DRUG LABEL: Herbomint Cough Drops
NDC: 57631-205 | Form: LOZENGE
Manufacturer: InvaTech Pharma Solutions LLC
Category: otc | Type: HUMAN OTC DRUG LABEL
Date: 20190522

ACTIVE INGREDIENTS: MENTHOL 9.99 mg/1 1
INACTIVE INGREDIENTS: CARDAMOM; CARAMEL; BASIL; LICORICE; ACACIA CATECHU WHOLE; MALABAR PLUM JUICE; CLOVE; EUCALYPTUS OIL; RAW SUGAR

Drug Facts

Active Ingredient

Menthol (From Mentha spicata) (in each 3gm Drop of Serving Size)....................................................9.99 mg

Uses

Natural way of calming cough and soothing sore throats

Warnings

Sore throat warnings: if sore throat is severe, persists for more than 2 days, is accompanied or followed by fever, headache, rash, swelling, nausea, or vomiting, consult a doctor promptly. These may be serious.
Do not use for children under 6 years of age unless directed by a doctor.

Ask a doctor before use if you have

- persistent or chronic cough such as occurs with smoking, asthma, or emphysema
- cough accompanied by excessive phlegm (mucus)

Stop use and ask a doctor if

- cough persists for more than 1 week, tends to recur, or is accompanied by fever, rash, or persistent headache. These could be signs of a serious condition.
- sore mouth does not improve in 7 days
- irritation, pain, or redness persist or worsens

Directions

- adults and children 6 years and over: dissolve 1 drop slowly in the mouth. Repeat every 2 hours as if needed or as directed by a doctor
- children under 6 years: ask a doctor
- do not bite or chew

Other information

Protect from heat and moisture

Inactive Ingredients

Holy Basil, Liquorice, Acacia catechu, Malabar, Cardamom, Clove, eucalyptus oil, caramel color q.s sugar base q.s

PURPOSE

Natural way of calming cough and soothing sore throats

OTC Principal Display Panel

Herbomint Cough Drops
100ct